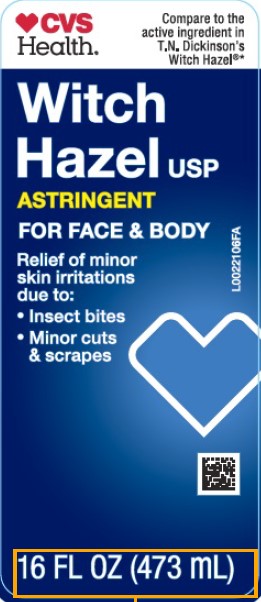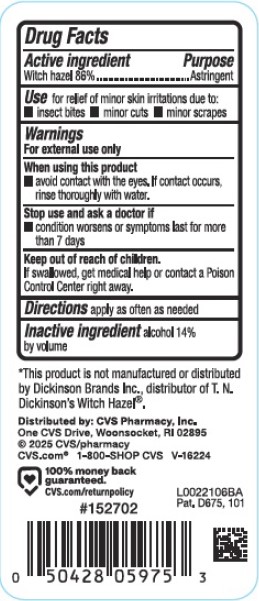 DRUG LABEL: Witch Hazel
NDC: 59779-045 | Form: LIQUID
Manufacturer: CVS Pharmacy, Inc.
Category: otc | Type: HUMAN OTC DRUG LABEL
Date: 20260203

ACTIVE INGREDIENTS: WITCH HAZEL 860 mg/1 mL
INACTIVE INGREDIENTS: ALCOHOL

CVS 822.001/822AA
Witch Hazel

Active ingredient

Witch Hazel 86%

Purpose

Astringent

Uses

for relief of minor skin irritations due to:

- insect bites
- minor cuts
- minor scrapes

Warnings

For external use only

When using this product

- avoid contact with the eyes. If contact occurs, rinse thoroughly with water.

Stop use and ask a doctor if

- condition worsens or symptoms persist for more than 7 days

Keep out of reach of children.

If swallowed, get medical help or contact a Poison Control Center right away.

Directions

apply as often as needed

Inactive ingredient

alcohol 14% by volume

Disclaimer

*This product is not manufactured or distributed by Dickinson Brands Inc., distributor of T.N. Dickinson's Witch Hazel®.

ADVERSE REACTION

Distributed By: CVS Pharmacy Inc.

One CVS Drive, Woonsocket, RI 02895

© 2025 CVS/pharmacy

CVS.com® 1-800-SHOP CVS V-16224

100% money back guaranteed.

CVS.com/returnpolicy

Pat. D675, 101

Principal display panel

CVS Health®

Compare to the active ingredient in T.N. Dickinson's Witch Hazel®*

Witch Hazel USP

ASTRINGENT

FOR FACE & BODY

Relief of minor skin irrations due to:

- Insect bites
- Minor cuts & scrapes

16 FL OZ (473 mL)